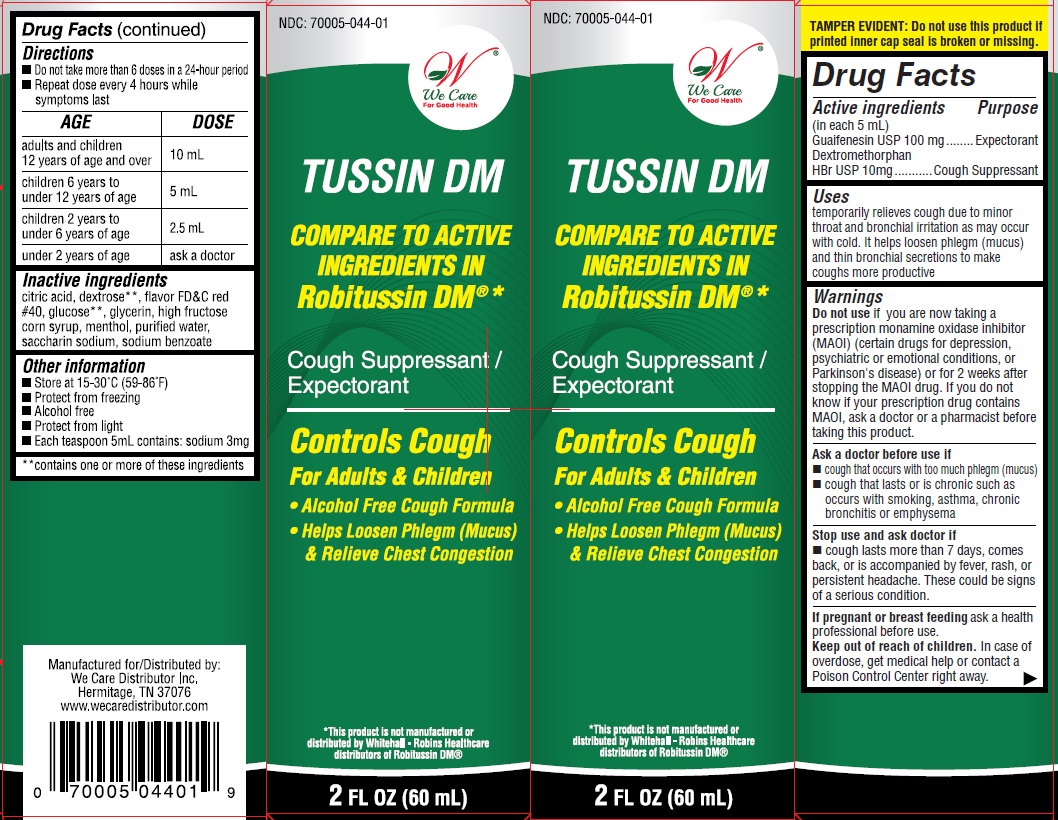 DRUG LABEL: Cough Suppressant and Expectorant DM
NDC: 70005-044 | Form: LIQUID
Manufacturer: We Care Distributor Inc.
Category: otc | Type: HUMAN OTC DRUG LABEL
Date: 20160802

ACTIVE INGREDIENTS: Dextromethorphan Hydrobromide 10 mg/5 mL; GUAIFENESIN 100 mg/5 mL
INACTIVE INGREDIENTS: CITRIC ACID MONOHYDRATE; DEXTROSE; GLYCERIN; HIGH FRUCTOSE CORN SYRUP; MENTHOL; SACCHARIN SODIUM; SODIUM BENZOATE; FD&C RED NO. 40

Drug Facts

Active ingredients

Dextromethorphan HBr, USP 10 mg
Guaifenesin, USP 100 mg

Purpose

Cough suppressant
Expectorant

Uses

temporarily relieves cough due to minor throat and bronchial irritation as may occur with cold. It helps helps loosen phlegm (mucus) and thin bronchial secretions to make coughs more productive

Warnings

Do not use if you are now taking a prescription monoamine oxidase inhibitor (MAOI) (certain drugs for depression, psychiatric or emotional conditions, or Parkinson's disease), or for 2 weeks after stopping the MAOI drug. If you do not know if your prescription drug contains an MAOI, ask a doctor or pharmacist before taking this product.

Ask a doctor before use if

- cough that occurs with too much phlegm (mucus)
- cough that lasts or is chronic such as occurs with smoking, asthma, chronic bronchitis or emphysema

Stop use and ask a doctor if

cough lasts more than 7 days, comes back, or accompanied by fever, rash, or persistant headache.

These could be signs of a serious condition.

If pregnant or breast-feeding,

ask a health professional before use.

Keep out of the reach of children.

In case of accidental overdose, get medical help or contact a Poison Control Center right away.

Directions

- Do not take more than 6 doses in a 24-hour period
- Repeat dose every 4 hours while symptoms last

AGE DOSE

adults and children

12 years of age and over 10 mL
children 6 years to

under 12 years of age 5 mL

children 2 years to

under 6 years of age 2.5 mL

children under

under 2 years of age ask a doctor

Other information

- Store at 15-30°C (59-86°F)
- Protect from freezing
- Alcohol free
- Protect from light
- Each teaspoon 5mL contains: Sodium 3 mg

Inactive ingredients

citric acid, dextrose**, flavor, FD&C red #40, glucose, glycerin, high fructose corn syrup, menthol, purified water, saccharin sodium,
sodium benzoate

** contains one or more of these ingredients

Principal Display Panel

Compare to the Active Ingredients in Robitussin DM

Dextromethorphan HBr, 10 mg - guaifenesin, 100 mg

cough suppressant, expectorant

Non-Drowsy

Alcohol Free

Relieves- coughs, chest congestion and mucus

2 FL Oz (60 mL)